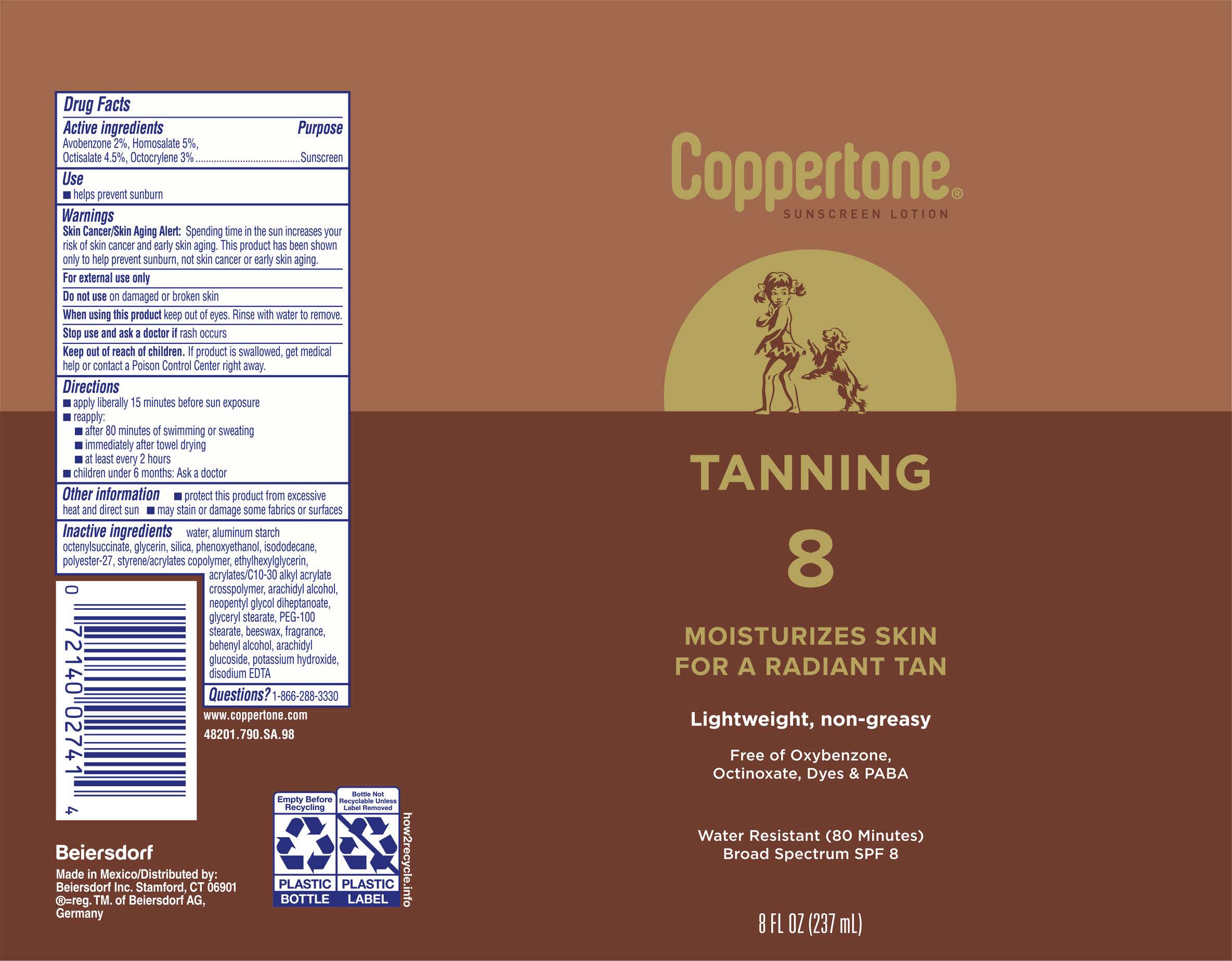 DRUG LABEL: Coppertone Tanning Sunscreen SPF 8
NDC: 66800-7034 | Form: LOTION
Manufacturer: Beiersdorf Inc
Category: otc | Type: HUMAN OTC DRUG LABEL
Date: 20251217

ACTIVE INGREDIENTS: OCTISALATE 4.5 g/100 g; OCTOCRYLENE 3 g/100 g; AVOBENZONE 2 g/100 g; HOMOSALATE 5 g/100 g
INACTIVE INGREDIENTS: WATER; STYRENE/ACRYLAMIDE COPOLYMER (500000 MW); ETHYLHEXYLGLYCERIN; GLYCERYL STEARATE SE; ARACHIDYL GLUCOSIDE; NEOPENTYL GLYCOL DIHEPTANOATE; FRAGRANCE FLORAL ORC0902236; DISODIUM EDTA-COPPER; SILICON DIOXIDE; POLYESTER-7; PEG-100 STEARATE; SYNTHETIC BEESWAX; ALUMINUM STARCH OCTENYLSUCCINATE; GLYCERIN; POTASSIUM HYDROXIDE; PHENOXYETHANOL; ISODODECANE; ACRYLATES/C10-30 ALKYL ACRYLATE CROSSPOLYMER (60000 MPA.S); ARACHIDYL ALCOHOL; DOCOSANOL

Coppertone Tanning Lotion SPF 8

Active ingredients

Avobenzone 2%, Homosalate 5%, Octisalate 4.5%, Octocrylene 3%

Purpose

Sunscreen

Use

■ helps prevent sunburn

Warnings

Skin Cancer/Skin Aging Alert:Spending time in the sun increases your risk of skin cancer and early skin aging. This product has been shown only to help prevent sunburn, not skin cancer or early skin aging.

For external use only

Do not useon damaged or broken skin

WHEN USING

When using this productkeep out of eyes. Rinse with water to remove.

Stop use and ask a doctor if rash occurs

Keep out of reach of children.If product is swallowed, get medical help or contact a Poison Control Center right away.

Directions

■ apply liberally 15 minutes before sun exposure

■ reapply:

■ after 80 minutes of swimming or sweating

■ immediately after towel drying

■ at least every 2 hours

■ children under 6 months: Ask a doctor

Other information

■ protect this product from excessive heat and direct sun

■ may stain or damage some fabrics or surfaces

Inactive ingredients

water, aluminum starch octenylsuccinate, glycerin, silica, phenoxyethanol, isododecane, polyester-27, styrene/acrylates copolymer, ethylhexylglycerin, acrylates/C10-30 alkyl acrylate crosspolymer, arachidyl alcohol, neopentyl glycol diheptanoate, glyceryl stearate, PEG-100 stearate, beeswax, fragrance, behenyl alcohol, arachidyl glucoside, potassium hydroxide, disodium EDTA

Questions?

1-866-288-3330

PACKAGE LABEL

Coppertone Sunscreen Lotion

Tanning 8

Moisturizes Skin for a Radiant Tan

Lightweight, non-greasy

Free of Oxybenzone, Octinoxate, Dyes & PABA

Water Resistant (80 Minutes)

Broad Spectrum SPF 8